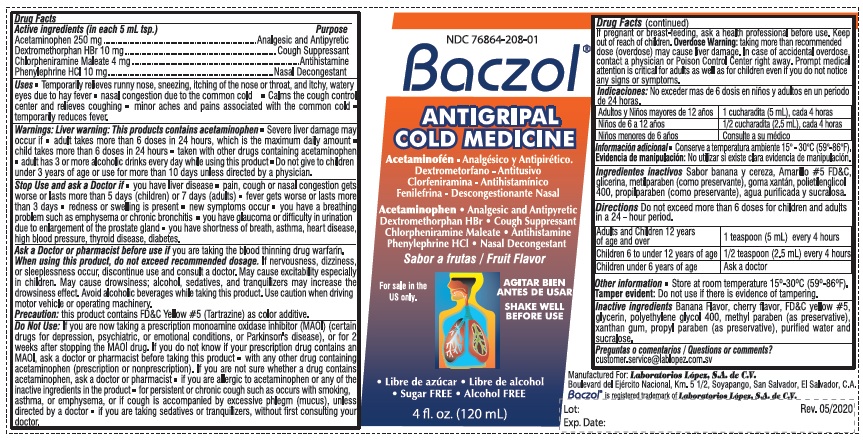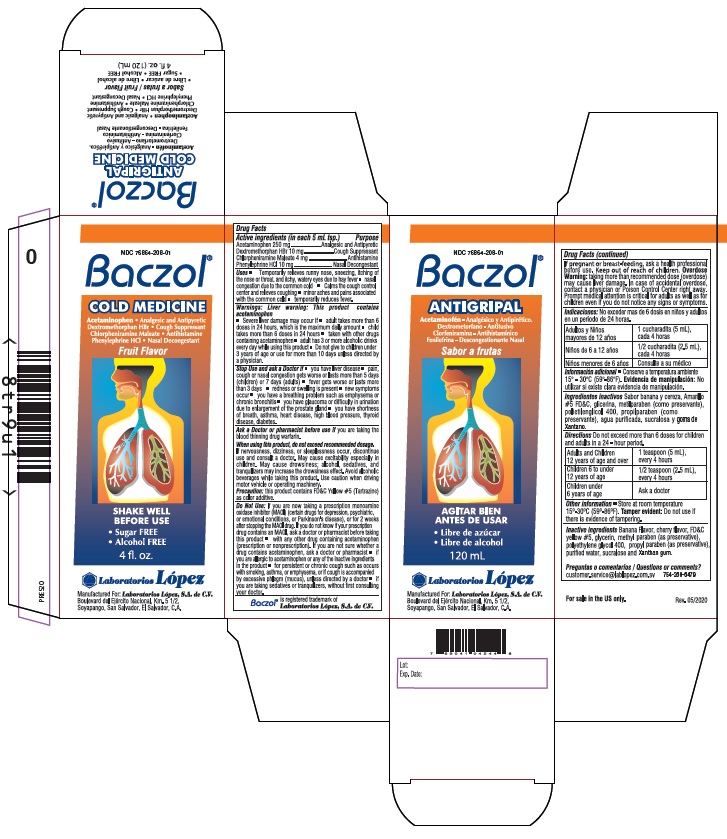 DRUG LABEL: BACZOL COLD MEDICINE
NDC: 76864-208 | Form: SYRUP
Manufacturer: Procaps S.A. de C.V.
Category: otc | Type: HUMAN OTC DRUG LABEL
Date: 20241227

ACTIVE INGREDIENTS: ACETAMINOPHEN 250 mg/5 mL; DEXTROMETHORPHAN HYDROBROMIDE 10 mg/5 mL; CHLORPHENIRAMINE MALEATE 4 mg/5 mL; PHENYLEPHRINE HYDROCHLORIDE 10 mg/5 mL
INACTIVE INGREDIENTS: FD&C YELLOW NO. 5; GLYCERIN; METHYLPARABEN; POLYETHYLENE GLYCOL 400; PROPYLPARABEN; WATER; SUCRALOSE; XANTHAN GUM

BACZOL COLD (Lex)

Drug Facts

Active ingredients (in each 5 mL tsp.)
Acetaminophen 250 mg
Dextromethorphan HBr 10 mg
Chlorpheniramine Maleate 4 mg
Phenylephrine HCl 10 mg

Purpose
Acetaminophen .................... Analgesic and Antipyretic
Dextromethorphan HBr ....................Cough Suppressant
Chlorpheniramine Maleate .........................Antihistamine
Phenylephrine HCl ........................ Nasal Decongestant

INDICATIONS AND USAGE

Uses • Temporarily relieves runny nose, sneezing, itching of
the nose or throat, and itchy, watery eyes due to hay fever • nasal
congestion due to the common cold • Calms the cough control
center and relieves coughing • minor aches and pains associated
with the common cold • temporarily reduces fever.

Warnings: Liver warning: This product contains
acetaminophen
• Severe liver damage may occur if • adult takes more than 6
doses in 24 hours, which is the maximum daily amount •child
takes more than 6 doses in 24 hours • taken with other drugs
containing acetaminophen• adult has 3 or more alcoholic drinks
every day while using this product • Do not give to children
under 3 years of age or use for more than 10 days unless directed by
a physician.

Stop Use and ask a Doctor if • you have liver disease • pain, cough or nasal congestion gets
worse or lasts more than 5 days (children) or 7 days (adults) • fever gets worse or lasts more
than 3 days • redness or swelling is present • new symptoms occur • you have a breathing
problem such as emphysema or chronic bronchitis • you have glaucoma or difficulty in urination
due to enlargement of the prostate gland • you have shortness of breath, asthma, heart disease,
high blood pressure, thyroid disease, diabetes.

Ask a Doctor or pharmacist before use if you are taking the blood thinning drug warfarin.

When using this product, do not exceed recommended dosage. If nervousness, dizziness,
or sleeplessness occur, discontinue use and consult a doctor. May cause excitability especially
in children. May cause drowsiness; alcohol, sedatives, and tranquilizers may increase the
drowsiness effect. Avoid alcoholic beverages while taking this product. Use caution when driving
motor vehicle or operating machinery.

PRECAUTIONS

Precaution: this product contains FD&C Yellow #5 (Tartrazine) as color additive.

Do Not Use:If you are now taking a prescription monoamine oxidase inhibitor (MAOI) (certain
drugs for depression, psychiatric, or emotional conditions, or Parkinson's disease), or for 2
weeks after stopping the MAOI drug. If you do not know if your prescription drug contains an
MAOI, ask a doctor or pharmacist before taking this product • with any other drug containing
acetaminophen (prescription or nonprescription). If you are not sure whether a drug contains
acetaminophen, ask a doctor or pharmacist • if you are allergic to acetaminophen or any of the
inactive ingredients in the product • for persistent or chronic cough such as occurs with smoking,
asthma, or emphysema, or if cough is accompanied by excessive phlegm (mucus), unless
directed by a doctor • if you are taking sedatives or tranquilizers, without first consulting your
doctor.

PREGNANCY OR BREAST FEEDING

If pregnant or breast-feeding, ask a health professional before use.

Keep out of reach of children.

OVERDOSAGE

Overdose Warning: taking more than recommended
dose (overdose) may cause liver damage. In case of accidental overdose,
contact a physician or Poison Control Center right away. Prompt medical
attention is critical for adults as well as for children even if you do not notice
any signs or symptoms.

DOSAGE AND ADMINISTRATION

Directions Do not exceed more than 6 doses for children and adults
in a 24 - hour period.

Adults and Children 12 years of age and over | 1 teaspoon (5 mL) every 4 hours
Children 6 to under 12 years of age | 1/2 teaspoon (2.5 mL) every 4 hours
Children under 6 years of age | Ask a doctor

Other information • Store at room temperature 15º-30ºC (59º-86ºF).
Tamper evident: Do not use if there is evidence of tampering.

Inactive ingredients Banana Flavor, cherry flavor, FD&C
yellow #5, glycerin, methyl paraben (as preservative),
polyethylene glycol 400, propyl paraben (as preservative),
purified water, sucralose and Xanthan gum.

Questions or comments?
customer.service@lablopez.com.sv 754-260-6479

Product Labeling

NDC 76864-208-01

Baczol®
COLD MEDICINE

Acetaminophen • Analgesic and Antipyretic
Dextromethorphan HBr • Cough Suppressant
Chlorpheniramine Maleate • Antihistamine
Phenylephrine HCl • Nasal Decongestant

Fruit Flavor

For sale in the
US only.

SHAKE WELL
BEFORE USE

• Sugar FREE • Alcohol FREE

4 fl.oz. (120 mL)

Manufactured For: Laboratorios López, S.A. de C.V.
Boulevard del Ejército Nacional, Km. 5 1/2,
Soyapango, San Salvador, El Salvador, C.A.

Baczol® is registered trademark of Laboratorios López, S.A. de C.V.

7 69041 04544 8

Lot: Rev. 05/2020

Exp. Date:

res